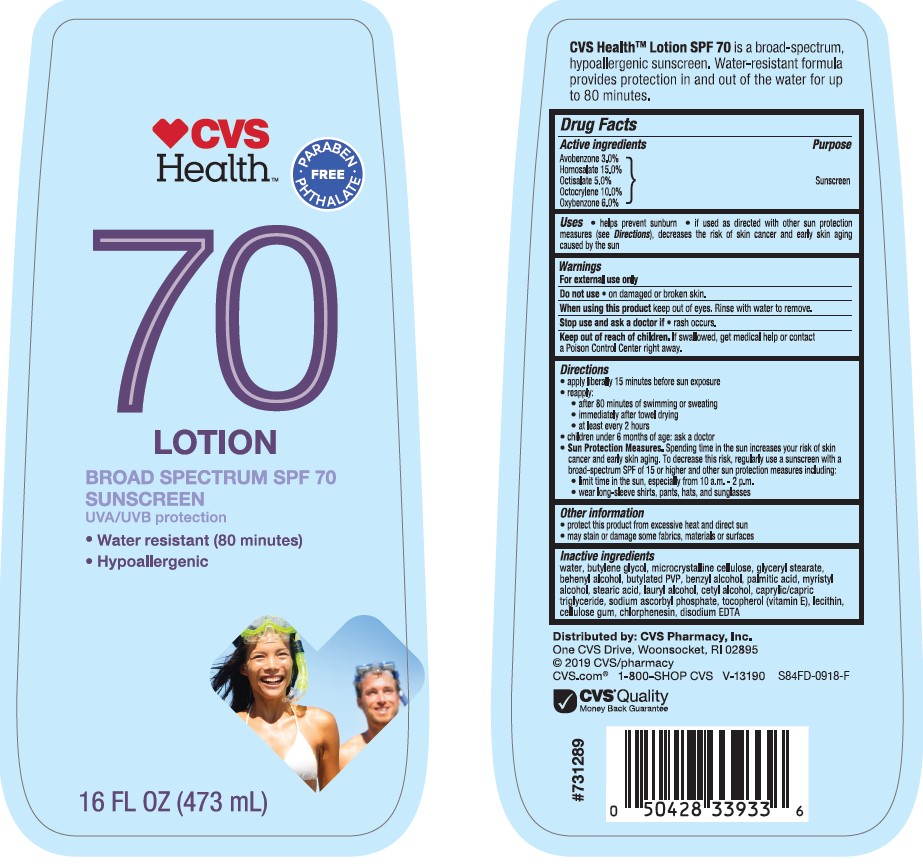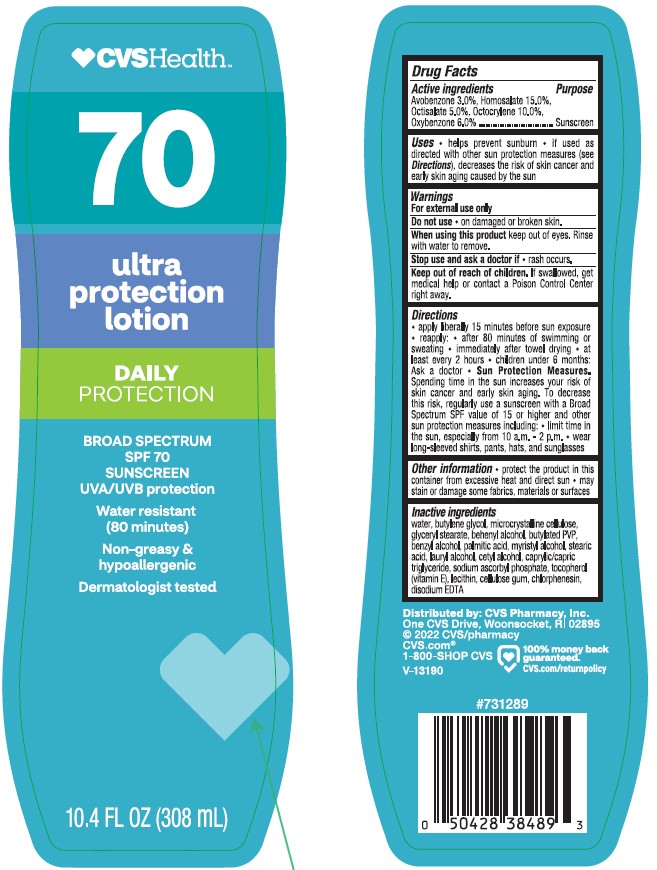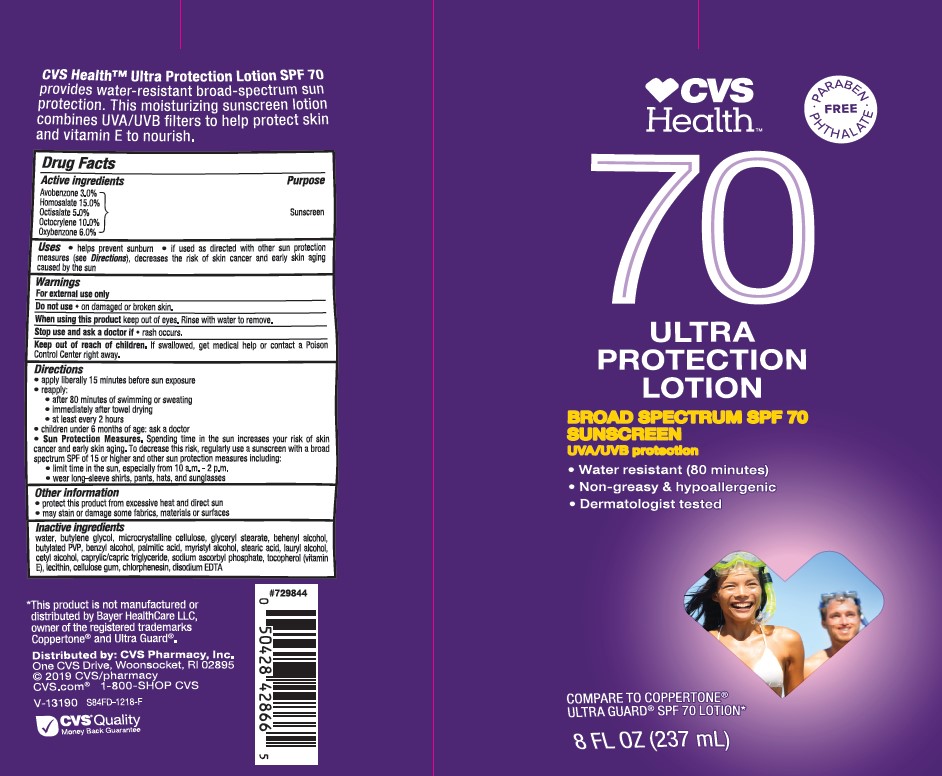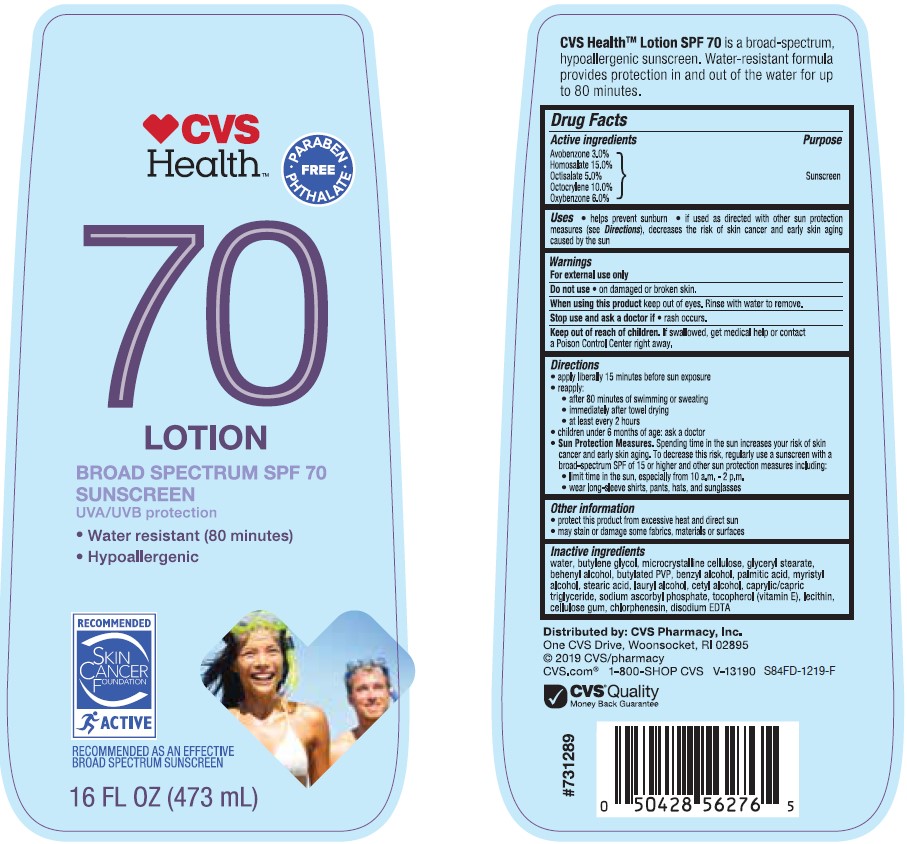 DRUG LABEL: CVS Health
NDC: 69842-164 | Form: LOTION
Manufacturer: CVS Pharmacy
Category: otc | Type: HUMAN OTC DRUG LABEL
Date: 20241022

ACTIVE INGREDIENTS: OCTOCRYLENE 100 mg/1 mL; OCTISALATE 50 mg/1 mL; HOMOSALATE 150 mg/1 mL; AVOBENZONE 30 mg/1 mL; OXYBENZONE 60 mg/1 mL
INACTIVE INGREDIENTS: .ALPHA.-TOCOPHEROL, DL-; EDETATE DISODIUM; WATER; BUTYLENE GLYCOL; MICROCRYSTALLINE CELLULOSE; GLYCERYL 1-STEARATE; DOCOSANOL; BENZYL ALCOHOL; CETYL ALCOHOL; MEDIUM-CHAIN TRIGLYCERIDES; STEARIC ACID; PALMITIC ACID; LAURYL ALCOHOL; MYRISTYL ALCOHOL; CARBOXYMETHYLCELLULOSE SODIUM; EGG PHOSPHOLIPIDS; CHLORPHENESIN; SODIUM ASCORBYL PHOSPHATE

CVS Health SPF 70 Sun Lotion

Active ingredients

Avobenzone 3.0%, Homosalate 15.0%, Octisalate 5.0%, Octocrylene 10.0%, Oxybenzone 6.0%

Purpose

Sunscreen

Uses

- helps prevent sunburn
- if used as directed with other sun protection measures (see Directions), decreases the risk of skin cancer and early skin aging caused by the sun

Warnings

For external use only

Do not use

- on damaged or broken skin

When using this product

keep out of eyes. Rinse with water to remove.

Stop use and ask doctor if

- rash occurs.

Keep out of reach of children.

If product is swallowed, get medical help or contact a Poison Control Center right away.

Directions

• apply liberally 15 minutes before sun exposure
reapply:
• after 80 minutes of swimming or sweating
• immediately after towel drying
• at least every 2 hours

• children under 6 months: Ask a doctor
Sun Protection Measures. Spending time in the sun increases your risk of skin cancer and early skin aging. To decrease this risk, regularly use a sunscreen with a Broad Spectrum SPF value of 15 or higher and other sun protection measures including:
• limit time in the sun, especially from 10 a.m. - 2 p.m.
• wear long-sleeved shirts, pants, hats, and sunglasses

Other information

• protect the product in this container from excessive heat and direct sun
• may stain or damage some fabrics, materials or surfaces

Inactive ingredients

Water, Butylene Glycol, Microcrystalline Cellulose, Glyceryl Stearate, Behenyl Alcohol, Butylated PVP, Benzyl Alcohol, Palmitic Acid, Myristyl Alcohol, Stearic Acid, Lauryl Alcohol, Cetyl Alcohol, Caprylic/Capric Triglyceride, Sodium Ascorbyl Phosphate, Tocopherol (Vitamin E), Lecithin, Retinyl Palmitate (Vitamin A), Cellulose Gum, Chlorphensin, Disodium EDTA